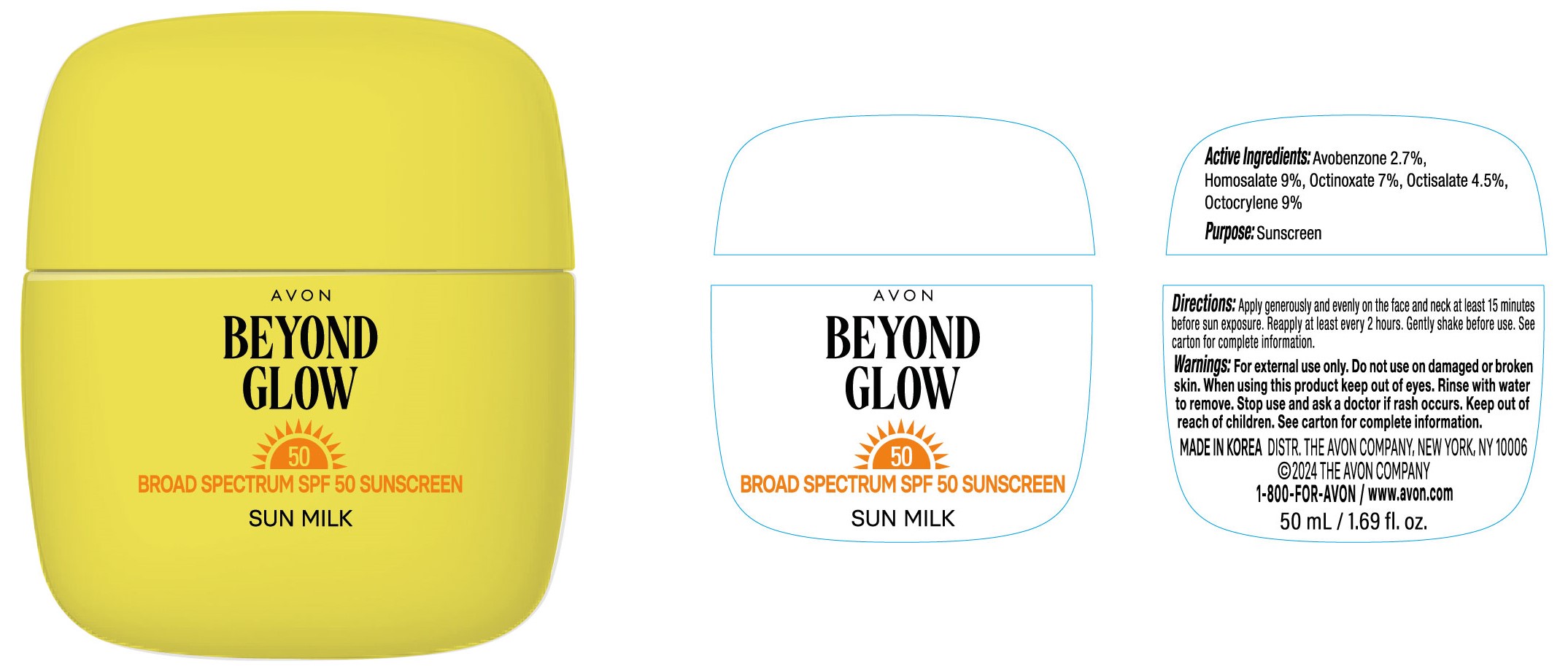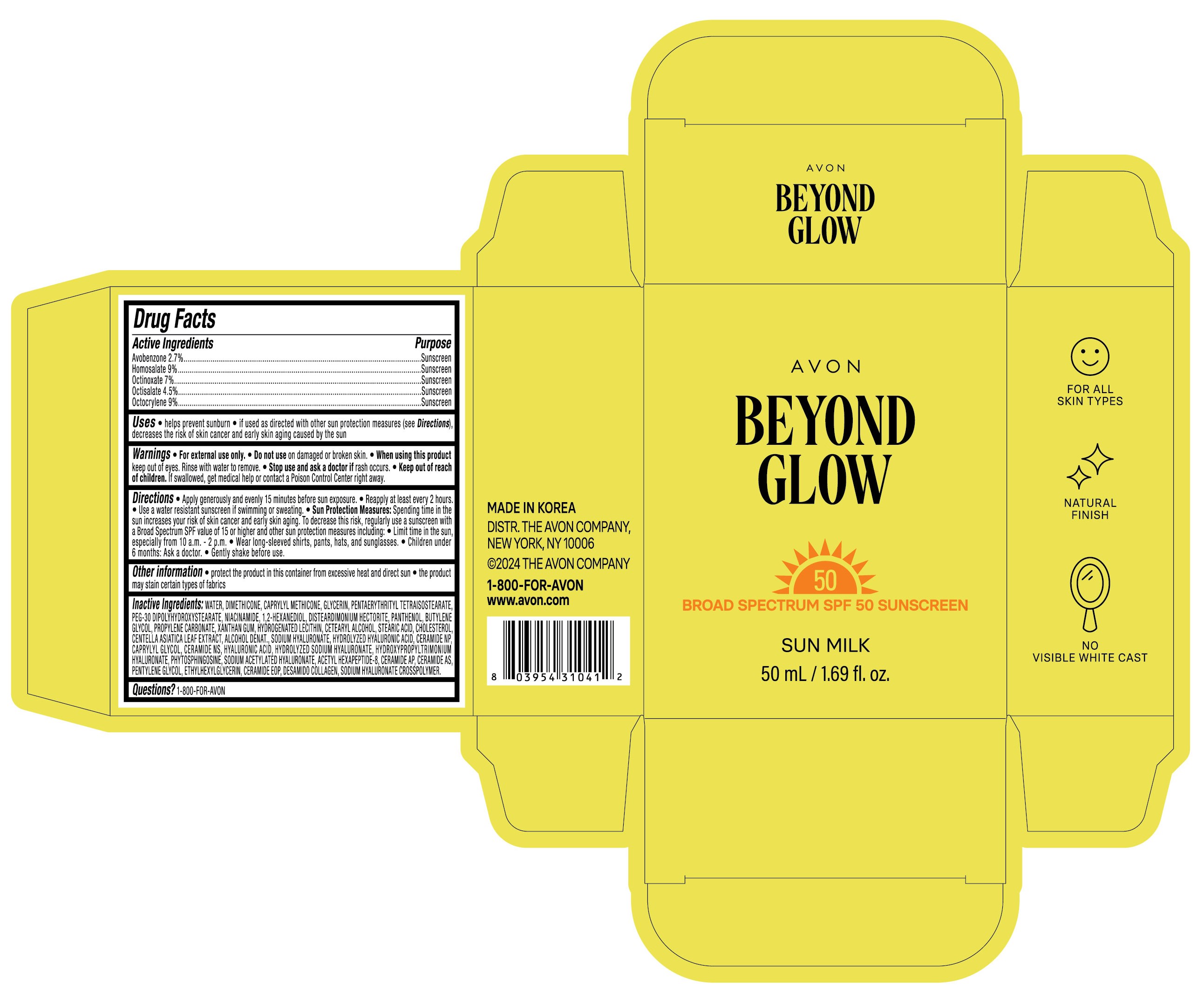 DRUG LABEL: AVON BEYOND GLOW SUN MILK
NDC: 53208-421 | Form: CREAM
Manufacturer: LG HOUSEHOLD & HEALTH CARE LTD.
Category: otc | Type: HUMAN OTC DRUG LABEL
Date: 20250620

ACTIVE INGREDIENTS: HOMOSALATE 90 mg/1 mL; OCTISALATE 45 mg/1 mL; AVOBENZONE 27 mg/1 mL; OCTINOXATE 70 mg/1 mL; OCTOCRYLENE 90 mg/1 mL
INACTIVE INGREDIENTS: DIMETHICONE; GLYCERIN; 1,2-HEXANEDIOL; CENTELLA ASIATICA LEAF; WATER; CHOLESTEROL; ACETYL HEXAPEPTIDE-8; CERAMIDE NP; BUTYLENE GLYCOL; XANTHAN GUM; CETEARYL ALCOHOL; CAPRYLYL GLYCOL; PHYTOSPHINGOSINE; PENTYLENE GLYCOL; ETHYLHEXYLGLYCERIN; SODIUM HYALURONATE; DEHYDRATED ALCOHOL; HYALURONIC ACID; STEARIC ACID; PANTHENOL; DISTEARDIMONIUM HECTORITE; PENTAERYTHRITYL TETRAISOSTEARATE; PEG-30 DIPOLYHYDROXYSTEARATE; CERAMIDE NS; PROPYLENE CARBONATE; NIACINAMIDE; CERAMIDE AP; CAPRYLYL METHICONE; SODIUM ACETYLATED HYALURONATE

Active Ingredients

Avobenzone 2.7%

Homosalate 9%

Octinoxate 7%

Octisalate 4.5%

Octocrylene 9%

Purpose

Sunscreen

Uses

- helps prevent sunburn
- if used as directed with other sun protection measures (see Directions), decreases the risk of skin cancer and early skin aging caused by the sun

Warnings

- For external use only.

- Do not use on damaged or broken skin.

- Stop use and ask a doctor if rash occurs.

When using

When using this product keep out of eyes. Rinse with water to remove.

Keep out of reach of children

DOSAGE AND ADMINISTRATION

If swallowed, get medical help or contact a Poison Control Center right away.

Directions

- Apply generously and evenly 15 minutes before sun exposure.
- Reapply at least every 2 hours.
- Use a water resistant sunscreen if swimming or sweating.
- Sun Protection Measures: Spending time in the sun increases your risk of skin cancer and early skin aging. To decrease this risk, regularly use a sunscreen with a Broad Spectrum SPF value of 15 or higher and other sun protection measures including:
  - Limit time in the sun, especially from 10 a.m. - 2 p.m.
  - Wear long-sleeved shirts, pants, hats, and sunglasses.
- Children under 6 months: Ask a doctor.
- Gently shake before use.

Other information

- protect the product in this container from excessive heat and direct sun
- the product may stain certain types of fabrics

Inactive ingredients

WATER, DIMETHICONE, CAPRYLYL METHICONE, GLYCERIN, PENTAERYTHRITYL TETRAISOSTEARATE, PEG-30 DIPOLYHYDROXYSTEARATE, NIACINAMIDE, 1,2-HEXANEDIOL, DISTEARDIMONIUM HECTORITE, PANTHENOL, BUTYLENE GLYCOL, PROPYLENE CARBONATE, XANTHAN GUM, HYDROGENATED LECITHIN, CETEARYL ALCOHOL, STEARIC ACID, CHOLESTEROL, CENTELLA ASIATICA LEAF EXTRACT, ALCOHOL DENAT., SODIUM HYALURONATE, HYDROLYZED HYALURONIC ACID, CERAMIDE NP, CAPRYLYL GLYCOL, CERAMIDE NS, HYALURONIC ACID, HYDROLYZED SODIUM HYALURONATE, HYDROXYPROPYLTRIMONIUM HYALURONATE, PHYTOSPHINGOSINE, SODIUM ACETYLATED HYALURONATE, ACETYL HEXAPEPTIDE-8, CERAMIDE AP, CERAMIDE AS, PENTYLENE GLYCOL, ETHYLHEXYLGLYCERIN, CERAMIDE EOP, DESAMIDO COLLAGEN, SODIUM HYALURONATE CROSSPOLYMER.

Questions?

1-800-FOR-AVON